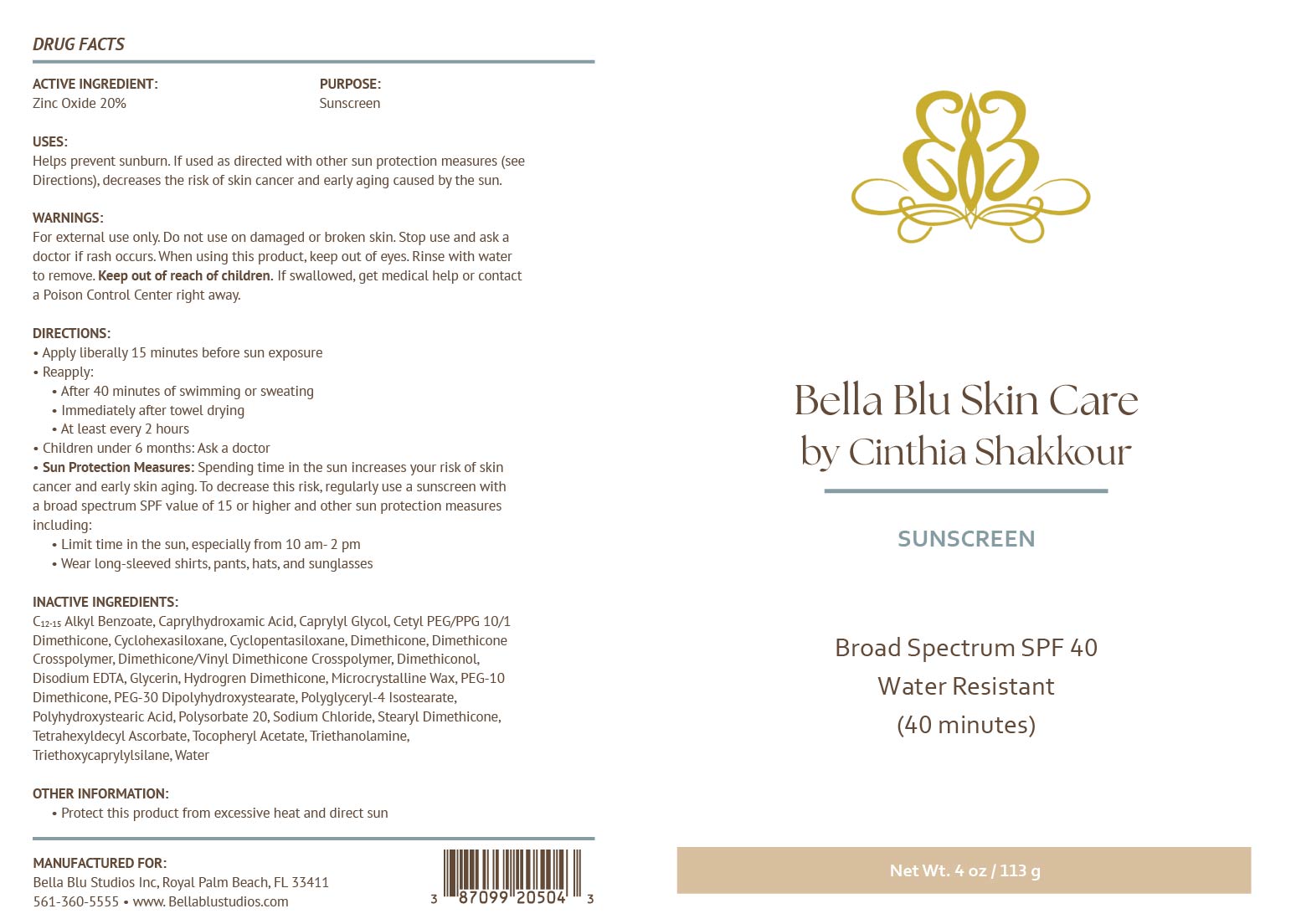 DRUG LABEL: Bella Blu Skin Care Non Tinted Sunscreen
NDC: 87099-205 | Form: CREAM
Manufacturer: BELLA BLU STUDIOS INC
Category: otc | Type: HUMAN OTC DRUG LABEL
Date: 20251217

ACTIVE INGREDIENTS: ZINC OXIDE 200 mg/1 g
INACTIVE INGREDIENTS: C12-15 ALKYL BENZOATE; CYCLOHEXASILOXANE; EDETATE DISODIUM ANHYDROUS; HYDROGEN DIMETHICONE (20 CST); POLYSORBATE 20; DIMETHICONOL (2000 CST); DIMETHICONE CROSSPOLYMER; POLYGLYCERYL-4 ISOSTEARATE; TRIETHANOLAMINE; CETYL PEG/PPG-10/1 DIMETHICONE (HLB 4); DIMETHICONE; TETRAHEXYLDECYL ASCORBATE; DIMETHICONE/VINYL DIMETHICONE CROSSPOLYMER (SOFT PARTICLE); GLYCERIN; PEG-10 DIMETHICONE (600 CST); ALPHA-TOCOPHEROL ACETATE; TRIETHOXYCAPRYLYLSILANE; WATER; PEG-30 DIPOLYHYDROXYSTEARATE; CAPRYLHYDROXAMIC ACID; MICROCRYSTALLINE WAX; STEARYL DIMETHICONE (400 MPA.S AT 50C); CAPRYLYL GLYCOL; CYCLOPENTASILOXANE; SODIUM CHLORIDE; POLYHYDROXYSTEARIC ACID (2300 MW)

Active Ingredients:

Zinc Oxide 20%

Purpose:

Sunscreen

Uses:

Helps Prevent Sunburn. If used as directed with other sun protection measures (see “Directions”), decreases the risk of skin cancer and early skin aging caused by the sun.

Warnings:

For external use only. Do not use on broken or damaged skin. Stop use and ask a doctor if rash occurs. When using this product, keep out of eyes. Rinse with water to remove. Keep out of reach of children. If swallowed, get medical help or contact a poison control center right away.

Warnings:

Keep out of reach of children

Directions:

Apply liberally 15 minutes before sun exposure. Use a water-resistant product if swimming or sweating. Reapply at least every 2 hours. Children under 6 months: Ask a doctor. Sun Protection Measures: Spending time in the sun increases your risk of skin cancer and early skin aging. To decrease this risk, regularly use a sunscreen with a Broad-Spectrum SPF value of 15 or higher and other sun protection measures including: Limit time in the sun, especially from 10 a.m. - 2 p.m. Wear long-sleeved shirts, pants, hats and sunglasses.

Inactive Ingredients:

C12-15 Alkyl Benzoate, Caprylhydroxamic Acid, Caprylyl Glycol, Cetyl PEG/PPG-10/1 Dimethicone, Cyclohexasiloxane, Cyclopentasiloxane, Dimethicone, Dimethicone Crosspolymer, Dimethicone/Vinyl Dimethicone Crosspolymer, Dimethiconol, Disodium EDTA, Glycerin, Hydrogen Dimethicone, Microcrystalline Wax, PEG-10 Dimethicone, PEG-30 Dipolyhydroxystearate, Polyglyceryl-4 Isostearate, Polyhydroxystearic Acid, Polysorbate 20, Sodium Chloride, Stearyl Dimethicone, Tetrahexyldecyl Ascorbate, Tocopheryl Acetate, Triethanolamine, Triethoxycaprylylsilane, Water

Other Information:

- Protect this product from excessive heat and direct sun